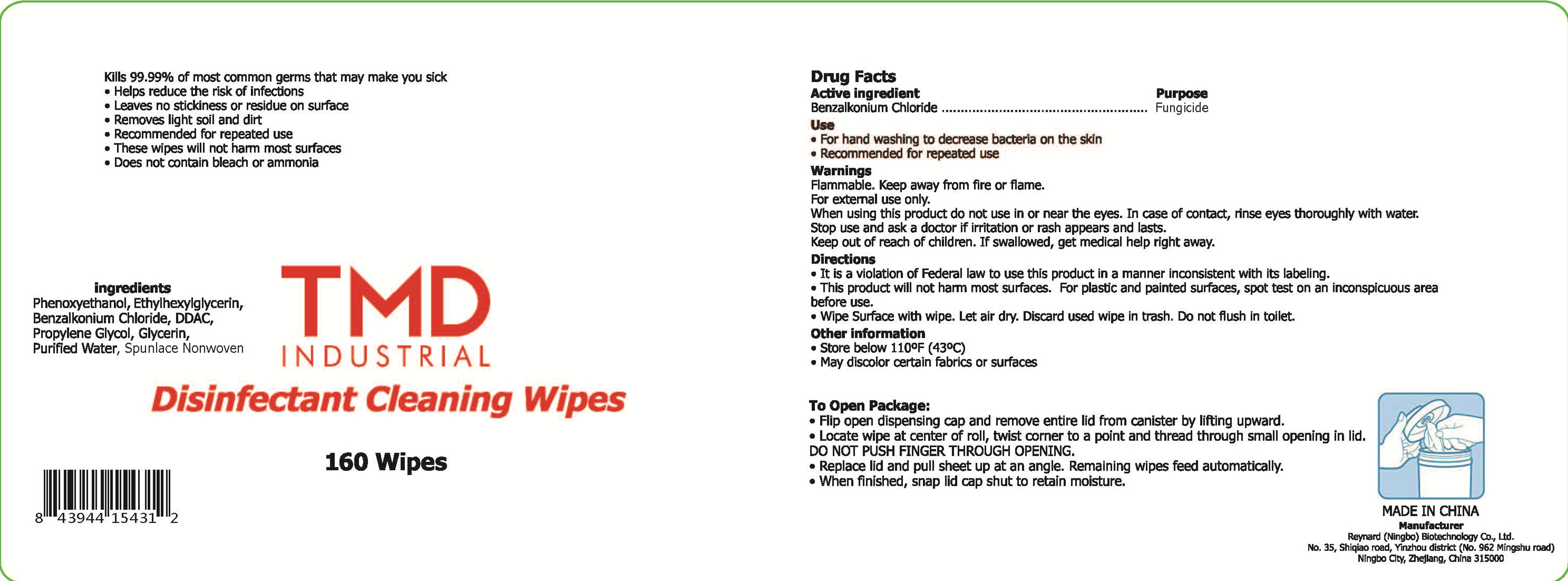 DRUG LABEL: Disinfectant  Cleaning  Wipes
NDC: 55485-004 | Form: CLOTH
Manufacturer: Reynard (Ningbo) Biotechnology Co., Ltd.
Category: otc | Type: HUMAN OTC DRUG LABEL
Date: 20200612

ACTIVE INGREDIENTS: BENZALKONIUM CHLORIDE 0.12 g/160 1; ETHYLHEXYLGLYCERIN 0.12 g/160 1; GLYCERIN 0.12 g/160 1; PHENOXYETHANOL 0.6 g/160 1; PROPYLENE GLYCOL 0.12 g/160 1; DIDECYLDIMONIUM CHLORIDE 0.24 g/160 1
INACTIVE INGREDIENTS: WATER

DOSAGE AND ADMINISTRATION

Store below 110°F (43°C)

INACTIVE INGREDIENT

Purified water

Spunlace non-woven

INDICATIONS AND USAGE

●It is a violation of Federal law to use this product in a manner inconsistent with its labeling.
●This product will not harm most surfaces. For plastic and painted surfaces, spot test on an inconspicuous area before use.
●Wipe Surface with wipe. Let air dry. Discard used wipe in trash. Do not fush in toilet.

ACTIVE INGREDIENT

phenoxyethanol

Ethylhexylglycerin

Benzalkonium chloride

DDAC

Propylene glycol

glycerin

keep out of reach of children

PURPOSE

Disinfection
Sterilization
No Rinseing

WARNINGS

1.Flammable. Keep away from fire or fiame.
2.For extermal use only.
3.When using this product do not use in or near the eyes. In case of contact, rinse eyes thoroughly with water.
4.Stop use and ask a doctor if iritation or rash appears and lasts.
5.Keep out of reach of children. If swallowed, get medical help right away.